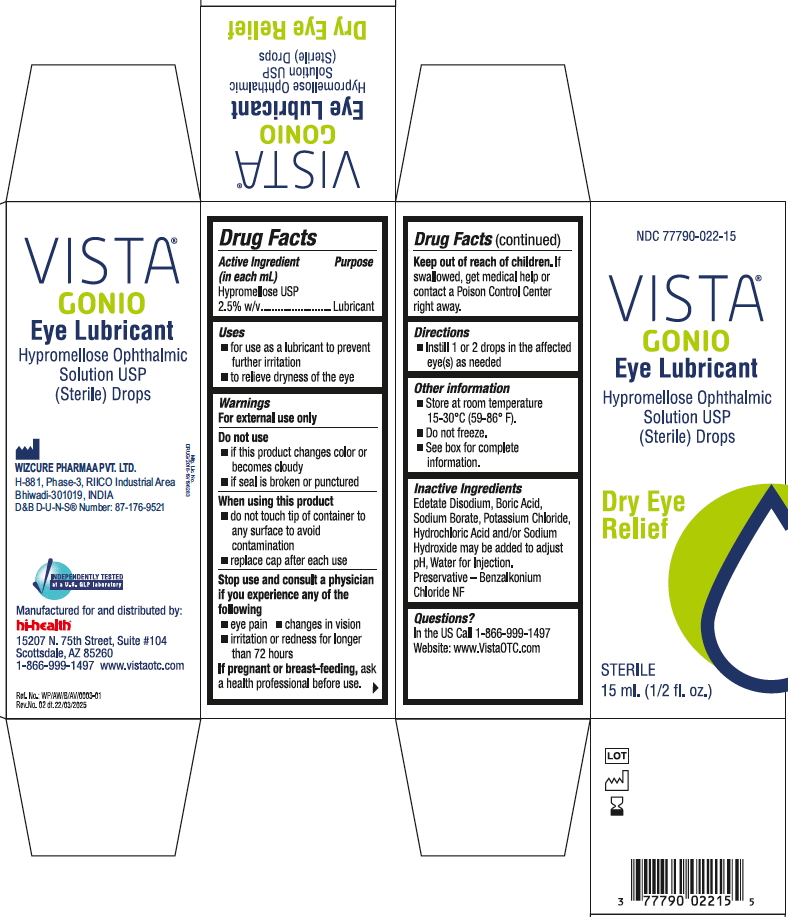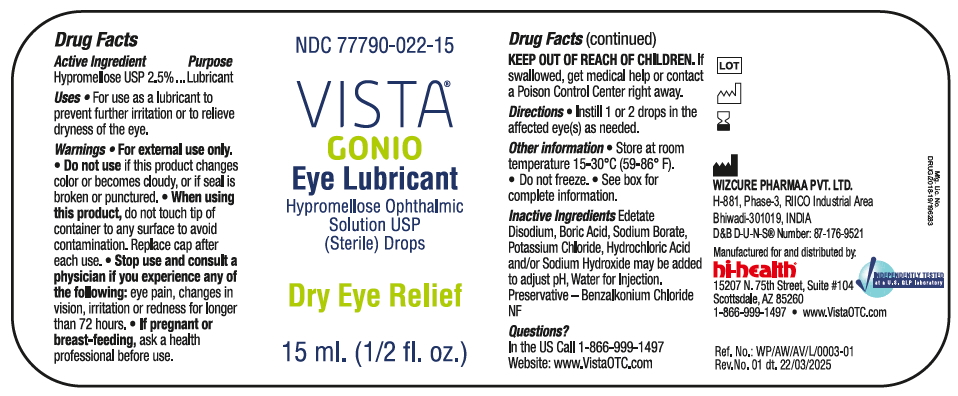 DRUG LABEL: Vista Gonio Eye Lubricant
NDC: 77790-022 | Form: SOLUTION
Manufacturer: Red Wedding LLC
Category: otc | Type: HUMAN OTC DRUG LABEL
Date: 20250325

ACTIVE INGREDIENTS: HYPROMELLOSE 2208 (100 MPA.S) 25 mg/15 mL
INACTIVE INGREDIENTS: HYDROCHLORIC ACID; SODIUM BORATE; BENZALKONIUM CHLORIDE; BORIC ACID; WATER; EDETATE DISODIUM; SODIUM HYDROXIDE; POTASSIUM CHLORIDE

Vista Gonio eye lubricant 15ml

Active ingredients

Hypromellose USP 2.5% w/v .....Lubricant

Use

For use as a lubricant to prevent further irritation or to relieve dryness of the eye.

Uses

- for use as a lubricant to prevent further irritation
- to relieve dryness of the eye

WARNINGS

Warnngs

For external use only

Do not use

■ if this product changes color or becomes cloudy

■ if seal is broken or punctured

When using this product

■ do not touch tip of container to any surface to avoid contamination

■ replace cap after each use

Stop use and consult a physician if you experience any of the following

■ eye pain

■ changes in vision

■ irritation or redness for longer than 72 hours

If pregnant or breast-feeding, ask a health professional before use.

Do not use

- if this product changes color or becomes cloudy
- if you are sensitive to any ingredient in this product

When using this product

- do not touch the tip of container to any surface to avoid contamination
- replace cap after each use

Stop use and consult a physician if you experience any of the following:

- eye pain
- changes in vision occur
- irritation or redness for longer than 72 hours

Keep out of reach of children

If swallowed, get medical help or contact a Poison Control Center right away

If pregnant or breastfeeding

ask a health professional before use.

Directions

- Instill 1 or 2 drops in the affected eye(s) as needed

Other information

- Store at room temperature 15-30^0C(59-86^0 F).
- do not freeze.
- See box for complete information

Inactive ingredients

Edetate Disodium, Boric Acid, Sodium Borate, Potassium Chloride, Hydrochloric Acid and/or Sodium Hxydroxide may be added to adjust pH, Water for Injection. Preservative - Benzalkonium Chloride NF.

Questions?

In the US Call 1-866-999-1497

Website: www.VistaOTC.com

PACKAGE LABEL

Vista Gonio - Box

Vista Gonio - Label